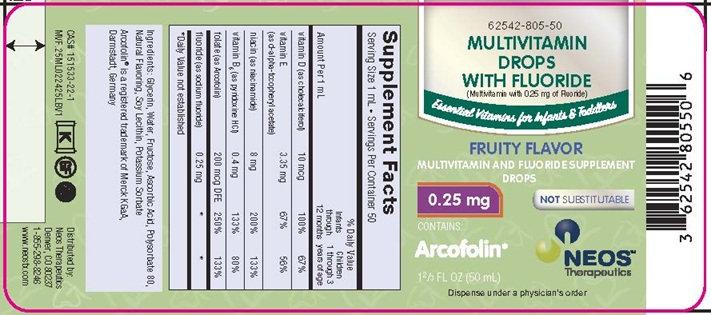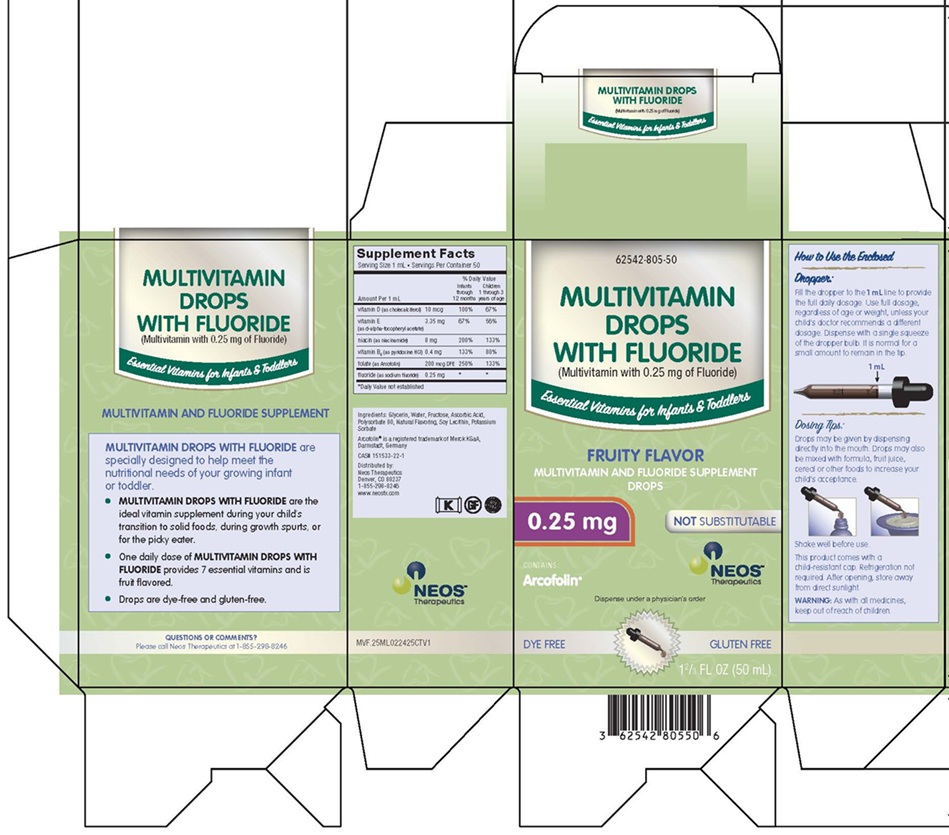 DRUG LABEL: MULTIVITAMIN DROPS WITH FLUORIDE
NDC: 62542-805 | Form: SUSPENSION/ DROPS
Manufacturer: Neos Therapeutics, LP
Category: other | Type: DIETARY SUPPLEMENT
Date: 20250416

ACTIVE INGREDIENTS: CHOLECALCIFEROL 10 ug/1 mL; .ALPHA.-TOCOPHEROL ACETATE, D- 3.35 mg/1 mL; NIACINAMIDE 8 mg/1 mL; PYRIDOXINE HYDROCHLORIDE 0.4 mg/1 mL; FOLIC ACID 200 ug/1 mL; SODIUM FLUORIDE 0.25 mg/1 mL
INACTIVE INGREDIENTS: GLYCERIN; WATER; FRUCTOSE; ASCORBIC ACID; POLYSORBATE 80; POTASSIUM SORBATE; SOYBEAN LECITHIN

MULTIVITAMIN DROPS WITH FLUORIDE DROPS

MULTIVITAMIN DROPS WITH FLUORIDE

(Multivitamin with 0.25 mg of Fluoride)

Fruity Flavor

Not Substitutable

Health Claim

Multivitamin and Fluoride Supplement Drops

Supplement Facts
Serving Size 1 mL • Servings Per Container 50
 |  |  | % Daily Value
Amount Per 1 mL |  |  | Infants through 12 months | Children 1 through 3 years of age
vitamin D (as cholecalciferol) |  | 10 mcg | 100% | 67%
vitamin E (as d-alpha-tocopheryl acetate) |  | 3.35 mg | 67% | 56%
niacin (as niacinamide) |  | 8 mg | 200% | 133%
vitamin B6 (as pyridoxine HCl) |  | 0.4 mg | 133% | 80%
folate (as Arcofolin) |  | 200 mcg DFE | 250% | 133%
fluoride (as sodium fluoride) |  | 0.25 mg | * | *

*Daily Value not established

Ingredients: Glycerin, Water, Fructose, Ascorbic Acid, Polysorbate 80, Natural Flavoring, Soy Lecithin, Potassium Sorbate

Contains: Arcofolin®

MULTIVITAMIN DROPS WITH FLUORIDE are specially designed to help meet the nutritional needs of your growing infant or toddler.

- MULTIVITAMIN DROPS WITH FLUORIDE are the ideal vitamin supplement during your child's transition to solid foods, during growth spurts, or for the picky eater.
- One daily dose of MULTIVITAMIN DROPS WITH FLUORIDE provides 7 essential vitamins and is fruit flavored.
- Drops are dye-free and gluten-free.

Dosage and Administration

How to Use the Enclosed

Dropper:

Fill the dropper to the 1 mL line to provide the full daily dosage. Use full dosage, regardless of age or weight, unless your child's doctor recommends a different dosage. Dispense with a single squeeze of the dropper bulb. It is normal for a small amount to remain in the tip.

Dosing Tips:

Drops may be given by dispensing directly into the mouth. Drops may also be mixed with formula, fruit juice, cereal or other foods to increase your child's acceptance.

Shake well before use.

This product comes with a child-resistant cap. Refrigeration not required. After opening, store away from direct sunlight.

Warning

WARNING: As with all medicines, keep out of reach of children.

Dispense under a physician’s order

Arcofolin® is a registered trademark of Merck KGaA, Darmstadt, Germany

CAS# 151533-22-1

Distributed by:
Neos Therapeutics
Denver, CO 80237
1-855-298-8246
www.neostx.com

PACKAGE LABEL

PRINCIPAL DISPLAY PANEL - MULTIVITAMIN DROPS WITH 0.25 MG OF FLUORIDE

62542-805-50

Essential Vitamins for Infants & Toddlers

FRUITY FLAVOR

MULTIVITAMIN AND FLUORIDE SUPPLEMENT DROPS

0.25 mg

NOT SUBSTITUTABLE

CONTAINS: Arcofolin

1 2/3 FL OZ (50 mL)

Neos Therapeutics